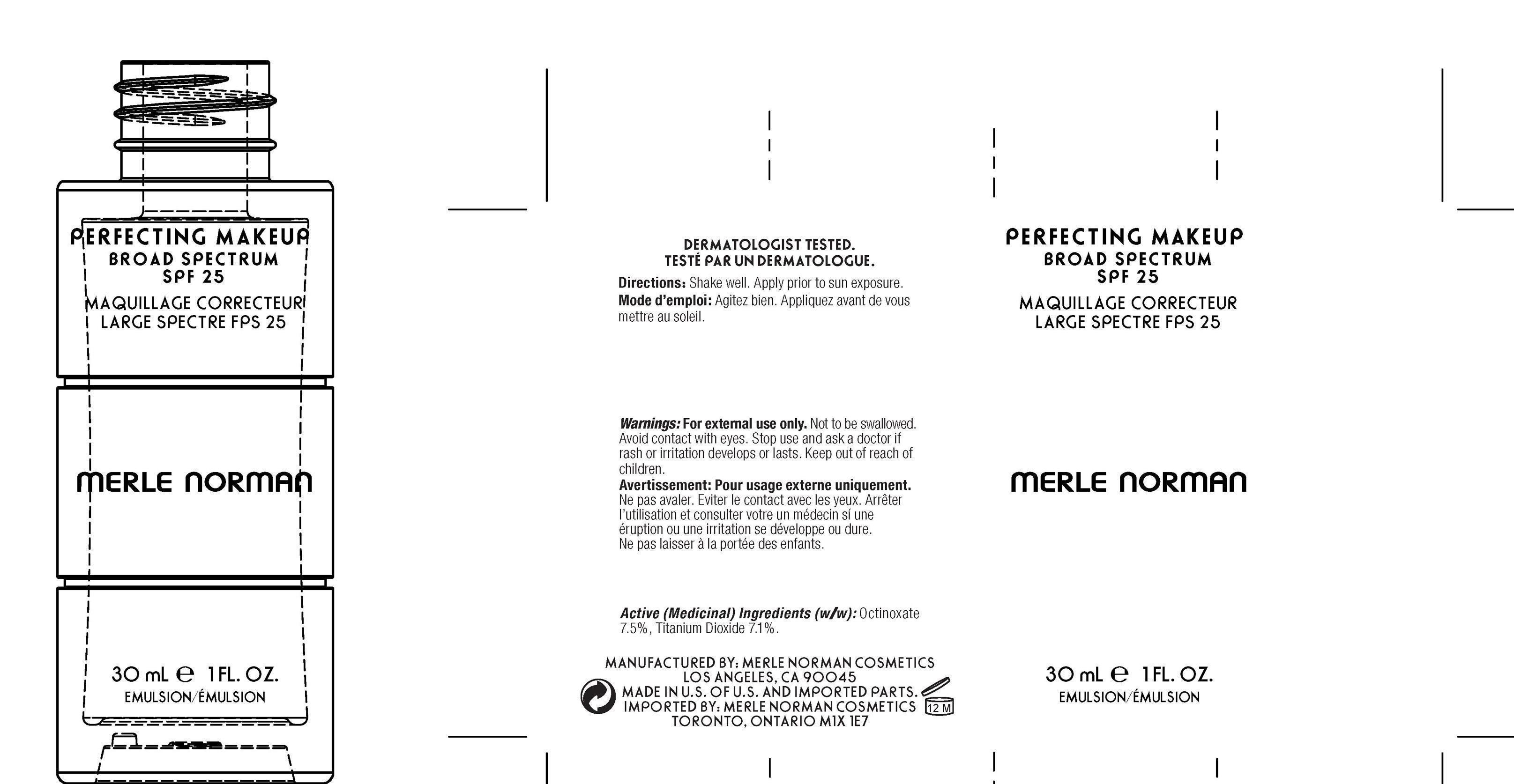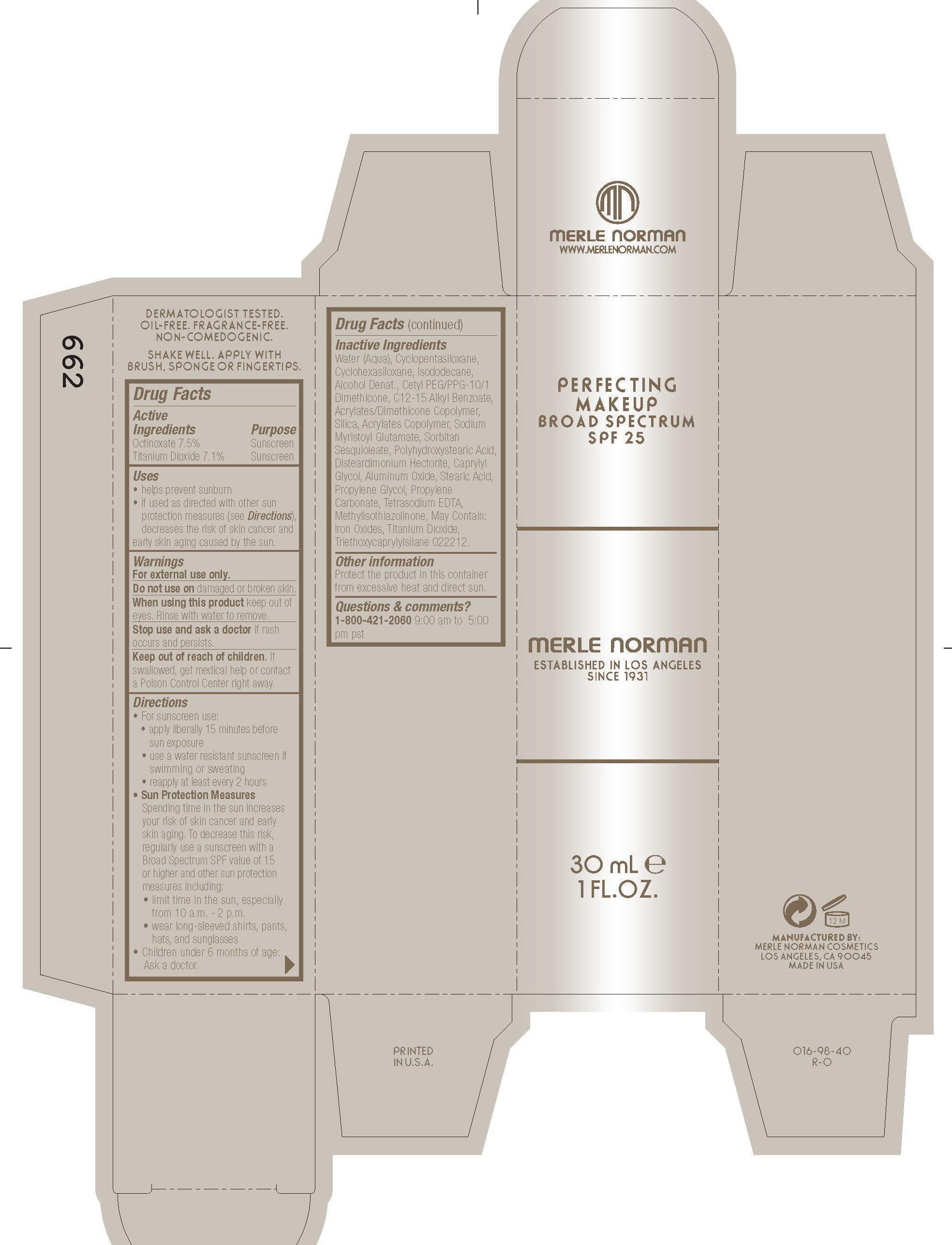 DRUG LABEL: Simply Beige Perfecting makeup SPF 25
NDC: 57627-129 | Form: EMULSION
Manufacturer: Merle Norman Cosmetics, Inc
Category: otc | Type: HUMAN OTC DRUG LABEL
Date: 20251119

ACTIVE INGREDIENTS: OCTINOXATE 30 g/30 mL; TITANIUM DIOXIDE 30 g/30 mL
INACTIVE INGREDIENTS: CYCLOMETHICONE 5; CYCLOMETHICONE 6; ISODODECANE; CETYL PEG/PPG-10/1 DIMETHICONE (HLB 2); ALKYL (C12-15) BENZOATE; SILICON DIOXIDE; SODIUM MYRISTOYL GLUTAMATE; SORBITAN SESQUIOLEATE; POLYHYDROXYSTEARIC ACID (2300 MW); CAPRYLYL GLYCOL; ALUMINUM OXIDE; STEARIC ACID; PROPYLENE GLYCOL; PROPYLENE CARBONATE; EDETATE DISODIUM; METHYLISOTHIAZOLINONE; FERRIC OXIDE RED; FERRIC OXIDE YELLOW; FERROSOFERRIC OXIDE; TRIETHOXYCAPRYLYLSILANE

Simply Beige Perfecting Makeup Broad Spectrum SPF 25

Active Ingredients purpose
Octinoxate 7.5% Sunscreen
Titanium Dioxide 7.1% Sunscreen

Uses
· helps prevent sunburn
· If used as directed with other sun protection measures (see Directions),
decreases the risk of skin cancer and early skin aging caused by the sun

· Keep out of reach of children. If swallowed, get medical help or
contact a Poison Control Center right away.

· Stop use and ask a doctor if rash occurs and persists

Warnings

· For external use only
· Do not use on damaged or broken skin
· When using this product keep out of eyes. Rinse with water to remove.

Directions
· Apply liberally 15 minutes before sun exposure
· Reapply at least every 2 hours
· Use a water resistant sunscreen if swimming or sweating
· Sun Protection Measures. Spending time in the sun increases your risk of skin
cancer and early skin aging. To decrease this risk, regularly use a sunscreen
with broad spectrum SPF of 15 or higher and other sun protection measures
including:
· limit time in the sun, especially from 10 a.m. - 2 p.m.
· wear long-sleeve shirts, pants, hats, and sunglasses
· Children under 6 months: Ask a doctor

Inactive Ingredients
Water (Aqua), Cyclopenta siloxane, Clyclohexasiloxane, Isododecane, Alcohol Denat.,
Cetyl PEG/PPG-10/1 Dimethicone, C12-15 Alkyl Benzoate, Acrylates/Dimethicone Copolymer,
Silica, Acrylates Copolymer, Sodium Myristoyl Glutamate, Sorbitan Sesquioleate,
Polyhydroxystearic Acid, Disteardimonium Hectorite, Caprylyl Glycol, Aluminum Oxide,
Stearic Acid, Propylene Glycol, Propylene Carbonate, Tetrasodium EDTA, Methylisothiazolinone,
May Contain: Iron Oxides, Titanium Dioxide, Triethoxycaprylylsilane

PACKAGE LABEL

Perfecting Makeup Broad Spectrum SPF 25

30 mL 1 Fl. Oz